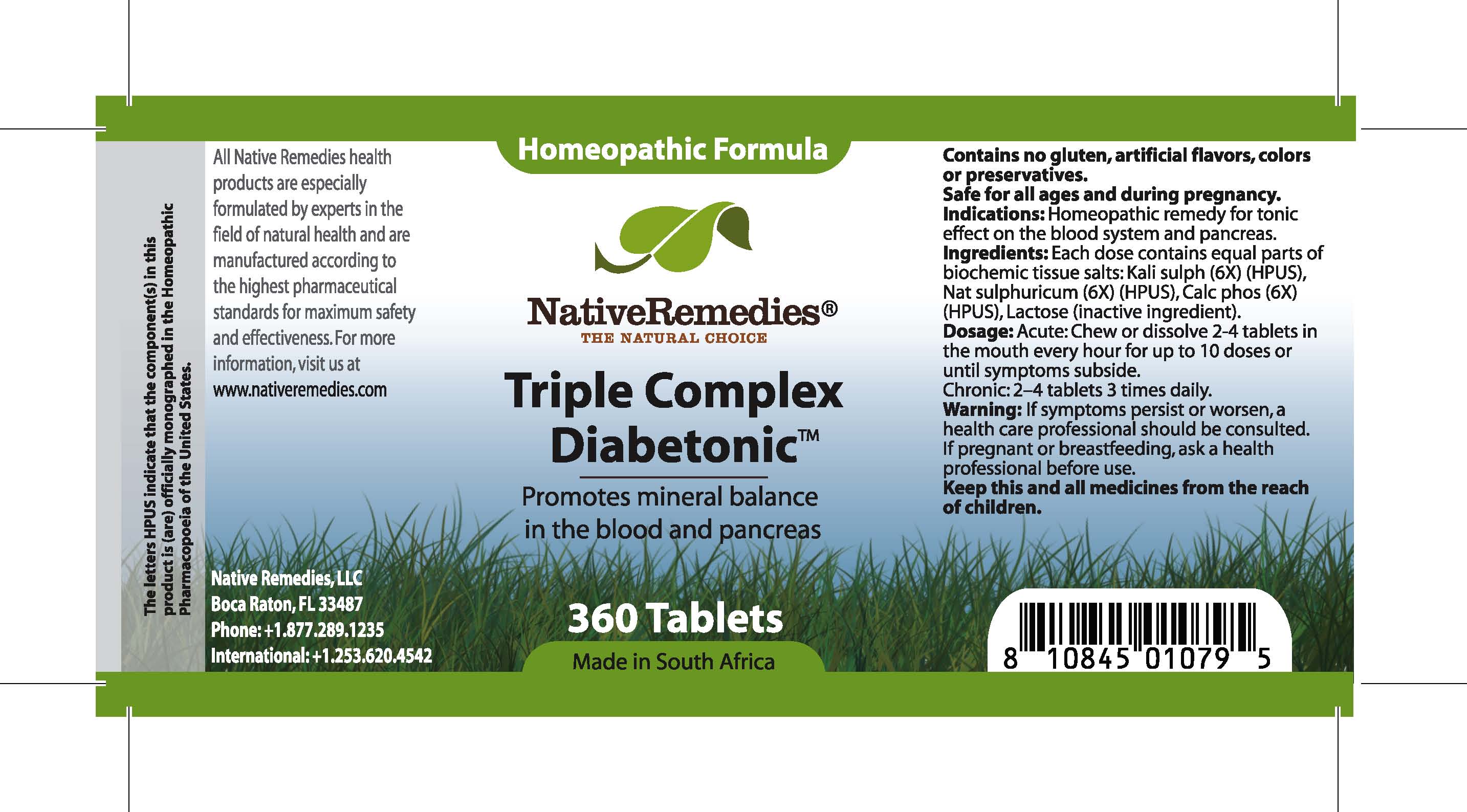 DRUG LABEL: Triple Complex Diabetonic 
NDC: 68647-134 | Form: TABLET
Manufacturer: Feelgood Health
Category: homeopathic | Type: HUMAN OTC DRUG LABEL
Date: 20100730

ACTIVE INGREDIENTS: POTASSIUM SULFATE 6 [hp_X]/1 1; SODIUM SULFATE 6 [hp_X]/1 1; TRIBASIC CALCIUM PHOSPHATE 6 [hp_X]/1 1
INACTIVE INGREDIENTS: LACTOSE

TRIPLE COMPLEX DIABETONIC

DESCRIPTION

Promotes mineral balance in the blood and pancreas

INDICATIONS AND USAGE

Indications: Homeopathic remedy for tonic effect on the blood system and pancreas.

DOSAGE AND ADMINISTRATION

Dosage: Acute: Chew or dissolve 2-4 tablets in the mouth every hour for up to 10 doses or until symptoms subside. Chronic: 2-4 tablets 3 times daily.

GENERAL PRECAUTIONS

Caution: If symptoms persist or worsen, a health care professional should be consulted. If pregnant or breastfeeding, ask a health professional before use. Keep this and all medicines from the reach of children.

ACTIVE INGREDIENT

Ingredients: Each dose contains equal parts of biochemic tissue salts: Kali sulph (6X) (HPUS), Nat sulphuricum (6X) (HPUS), Calc phos (6X) (HPUS)

Lactose (inactive ingredient).

PREGNANCY

If pregnant or breastfeeding, ask a health professional before use.

USER SAFETY WARNINGS

Contains no gluten, artificial flavors, colors or preservatives. Safe for all ages and during pregnancy.

PATIENT COUNSELING INFORMATION

All Native Remedies health products are especially formulated by experts in the field of natural health and are manufactured according to the highest pharmaceutical standards for maximum safety and effectiveness. For more information, visit us at www.nativeremedies.com

Distributed by

Native Remedies, LLC

6531 Park of Commerce Blvd.

Suite 160

Boca Raton, FL 33487

Phone: 1.877.289.1235

International: + 1.561.999.8857

The letters HPUS indicate that the component(s) in this product is (are) officially monographed in the Homeopathic Pharmacopoeia of the United States.